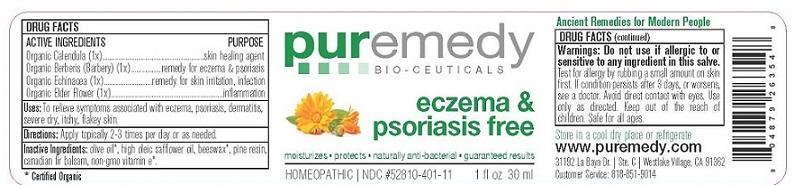 DRUG LABEL: ECZEMA AND PSORIASIS FREE
NDC: 52810-411 | Form: SALVE
Manufacturer: PUREMEDY
Category: homeopathic | Type: HUMAN OTC DRUG LABEL
Date: 20240111

ACTIVE INGREDIENTS: ECHINACEA ANGUSTIFOLIA 1 [hp_X]/100 mL; SAMBUCUS NIGRA FLOWER 1 [hp_X]/100 mL; CALENDULA OFFICINALIS FLOWER 1 [hp_X]/100 mL; BERBERIS VULGARIS WHOLE 1 [hp_X]/100 mL
INACTIVE INGREDIENTS: OLIVE OIL; SAFFLOWER OIL; YELLOW WAX; PINE NEEDLE OIL (PINUS SYLVESTRIS); ABIES BALSAMEA LEAF OIL; .ALPHA.-TOCOPHEROL

ECZEMA AND PSORIASIS FREE (52810-411)

ACTIVE INGREDIENTS

PINUS SILVESTRIS (1X) HPUS (PINE RESIN)

*SAMBUCUS NIGRA (2X) HPUS (ELDERBERRY)

*CALENDULA OFFICINALIS (2X) HPUS (MARIGOLD)

*BERBERIS AQUIFOLIUM (3X) HPUS (BARBERRY)

*ECHINACEA ANGUST. (6X) HPUS (ECHINACEA)

PURPOSE

PROPERTIES

SKIN PROTECTANT

ANTI-INFLAMMATORY

PROMOTES SKIN HEALING

ECZEMA AND PSORIASIS TREATMENT

PROMOTES SKIN HEALING

INDICATIONS AND USAGE

USES: TO RELIEVE SYMPTOMS ASSOCIATED WITH ECZEMA, PSORIASIS, DERMATITIS, SEVERE DRY ITCHY SKIN.

DOSAGE AND ADMINISTRATION

DIRECTIONS: APPLY TO AFFECTED AREA 3-4 TIMES PER DAY.

INACTIVE INGREDIENT

OTHER INGREDIENTS: ORGANIC OLIVE OIL, HIGH OLEIC SAFFLOWER OIL, ORGANIC BEESWAX, BALSAM FIR, ORGANIC SOY FREE VITAMIN E OIL.

WARNINGS

WARNING: TEST FOR ALLERGY BY RUBBING A SMALL AMOUNT ON SKIN FIRST. DO NOT USE IF ALLERGIC TO OR HYPER-SENSITIVE TO ANY INGREDIENT IN THIS SALVE. IF CONDITION PERSISTS OR WORSENS CONSULT YOUR HEALTH CARE PROVIDER. (* CERTIFIED ORGANIC INGREDIENTS)

KEEP OUT OF REACH OF CHILDREN.

OTHER SAFETY INFORMATION

STORE IN A COOL DRY PLACE OR REFRIGERATE